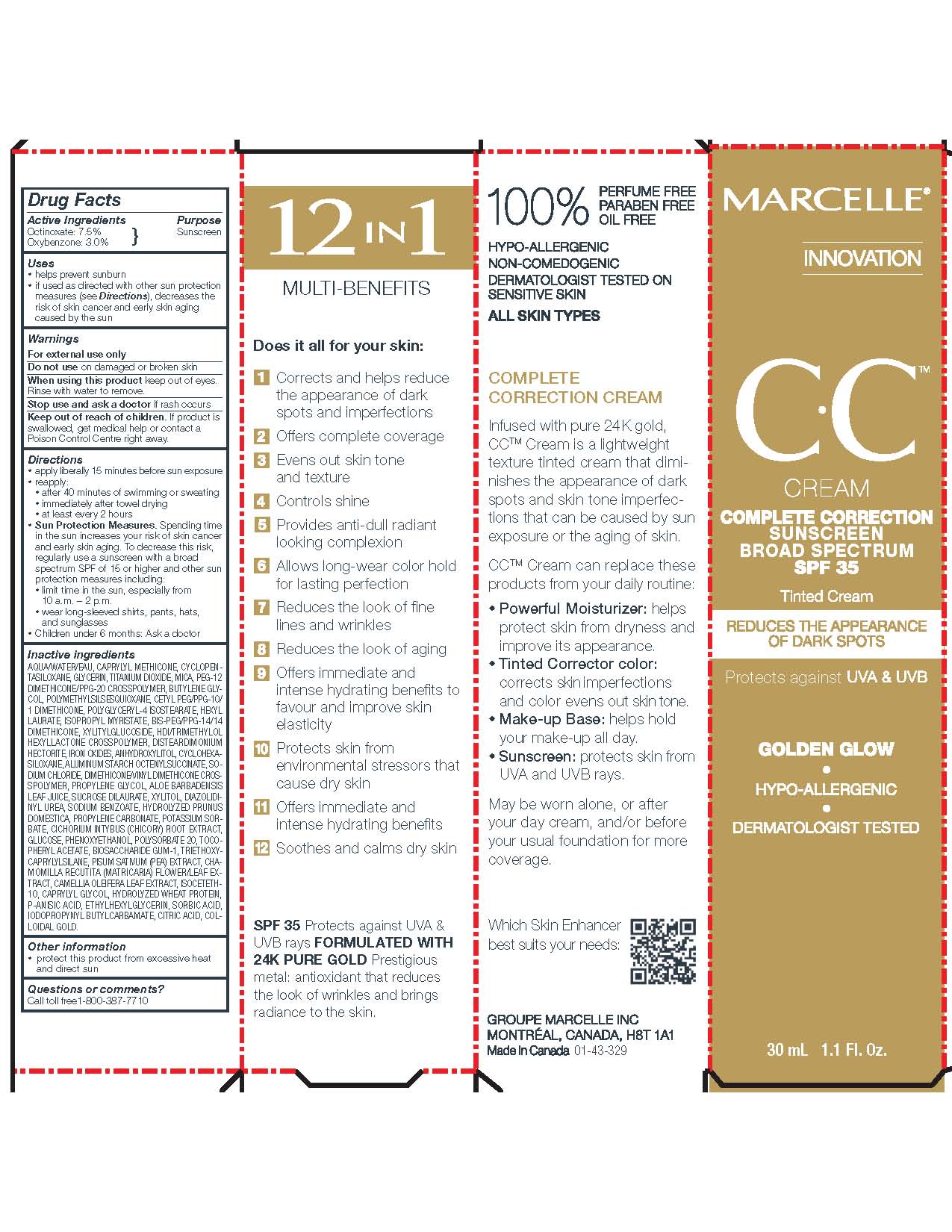 DRUG LABEL: Marcelle CC Cream Complete Correction Sunscreen Broad Spectrum SPF 35
NDC: 69922-003 | Form: CREAM
Manufacturer: Groupe Marcelle Inc.
Category: otc | Type: HUMAN OTC DRUG LABEL
Date: 20241003

ACTIVE INGREDIENTS: OCTINOXATE 0.525 g/7 mL; OXYBENZONE 0.21 g/7 mL
INACTIVE INGREDIENTS: WATER; CAPRYLYL TRISILOXANE; CYCLOMETHICONE 5; GLYCERIN; TITANIUM DIOXIDE; MICA; PEG-12 DIMETHICONE/PPG-20 CROSSPOLYMER; BUTYLENE GLYCOL; POLYMETHYLSILSESQUIOXANE (11 MICRONS); CETYL PEG/PPG-10/1 DIMETHICONE (HLB 2); POLYGLYCERYL-4 ISOSTEARATE; HEXYL LAURATE; ISOPROPYL MYRISTATE; BIS-PEG/PPG-14/14 DIMETHICONE; XYLITYLGLUCOSIDE; HEXAMETHYLENE DIISOCYANATE/TRIMETHYLOL HEXYLLACTONE CROSSPOLYMER; DISTEARDIMONIUM HECTORITE; FERRIC OXIDE RED; ANHYDROXYLITOL; CYCLOMETHICONE 6; ALUMINUM STARCH OCTENYLSUCCINATE; SODIUM CHLORIDE; DIMETHICONE/VINYL DIMETHICONE CROSSPOLYMER (SOFT PARTICLE); PROPYLENE GLYCOL; ALOE VERA LEAF; SUCROSE DILAURATE; XYLITOL; DIAZOLIDINYL UREA; SODIUM BENZOATE; PROPYLENE CARBONATE; POTASSIUM SORBATE; CHICORY ROOT; DEXTROSE; PHENOXYETHANOL; POLYSORBATE 20; .ALPHA.-TOCOPHEROL ACETATE; BIOSACCHARIDE GUM-1; TRIETHOXYCAPRYLYLSILANE; PEA; MATRICARIA RECUTITA FLOWERING TOP; CAMELLIA OLEIFERA LEAF; ISOCETETH-10; CAPRYLYL GLYCOL; HYDROLYZED WHEAT PROTEIN (ENZYMATIC; 3000 MW); P-ANISIC ACID; ETHYLHEXYLGLYCERIN; SORBIC ACID; IODOPROPYNYL BUTYLCARBAMATE; CITRIC ACID MONOHYDRATE; GOLD

Marcelle CC Cream Complete Correction Sunscreen Broad Spectrum SPF 35

Drug Facts

Active Ingredients Purpose

Octinoxate 7.5% Sunscreen

Oxybenzone 3.0% Sunscreen

Uses

- helps prevent sunburn
- if used as directed with other sun protection measures (see Directions), decreases the risk of skin cancer and early skin aging caused by the sun

Warnings

For external use only.

Do not use on damaged or broken skin.

When using this product keep out of eyes. Rinse with water to remove.

Stop use and ask a doctor if rash occurs.

Keep out of reach of children. If product is swallowed, get medical help or contact a Poison Control Centre right away.

Directions

- apply liberally 15 minutes before sun exposure
- reapply:

- after 40 minutes of swimming or sweating

- immediately after towel drying

- at least every 2 hours

- Sun Protection Measures. Spending time in the sun increases your risk of skin cancer and early skin aging. To decrease this risk, regularly use a sunscreen with a broad spectrum SPF of 15 or higher and other sun protection measures including:

- limit time in the sun, especially from 10 a.m. – 2 p.m.
- wear long-sleeved shirts, pants, hats, and sunglasses

- Children under 6 months: Ask a doctor

Inactive ingredients

AQUA/WATER/EAU, CAPRYLYL METHICONE, CYCLOPENTASILOXANE, GLYCERIN, TITANIUM DIOXIDE, MICA, PEG-12 DIMETHICONE/PPG-20 CROSSPOLYMER, BUTYLENE GLYCOL, POLYMETHYLSILSESQUIOXANE, CETYL PEG/PPG-10/1 DIMETHICONE, POLYGLYCERYL-4 ISOSTEARATE, HEXYL LAURATE, ISOPROPYL MYRISTATE, BIS-PEG/PPG-14/14 DIMETHICONE, XYLITYLGLUCOSIDE, HDI/TRIMETHYLOL HEXYLLACTONE CROSSPOLYMER, DISTEARDIMONIUM HECTORITE, IRON OXIDES, ANHYDROXYLITOL, CYCLOHEXASILOXANE, ALUMINUM STARCH OCTENYLSUCCINATE, SODIUM CHLORIDE, DIMETHICONE/VINYL DIMETHICONE CROSSPOLYMER, PROPYLENE GLYCOL, ALOE BARBADENSIS
LEAF JUICE, SUCROSE DILAURATE, XYLITOL, DIAZOLIDINYL UREA, SODIUM BENZOATE, HYDROLYZED PRUNUS DOMESTICA, PROPYLENE CARBONATE, POTASSIUM SORBATE, CICHORIUM INTYBUS (CHICORY) ROOT EXTRACT, GLUCOSE, PHENOXYETHANOL, POLYSORBATE 20, TOCOPHERYL ACETATE, BIOSACCHARIDE GUM-1, TRIETHOXYCAPRYLYLSILANE, PISUM SATIVUM (PEA) EXTRACT, CHAMOMILLA RECUTITA (MATRICARIA) FLOWER/LEAF EXTRACT, CAMELLIA OLEIFERA LEAF EXTRACT, ISOCETETH-10, CAPRYLYL GLYCOL, HYDROLYZED WHEAT PROTEIN, P-ANISIC ACID, ETHYLHEXYLGLYCERIN, SORBIC ACID, IODOPROPYNYL BUTYLCARBAMATE, CITRIC ACID, COLLOIDAL GOLD.

Other information

- protect this product from excessive heat and direct sun

Questions or comments?

Call toll free 1-800-387-7710

Principal Display Panel - 30 mL 1.1 Fl.Oz.

Marcelle CC Cream Complete Correction Sunscreen Broad Spectrum SPF